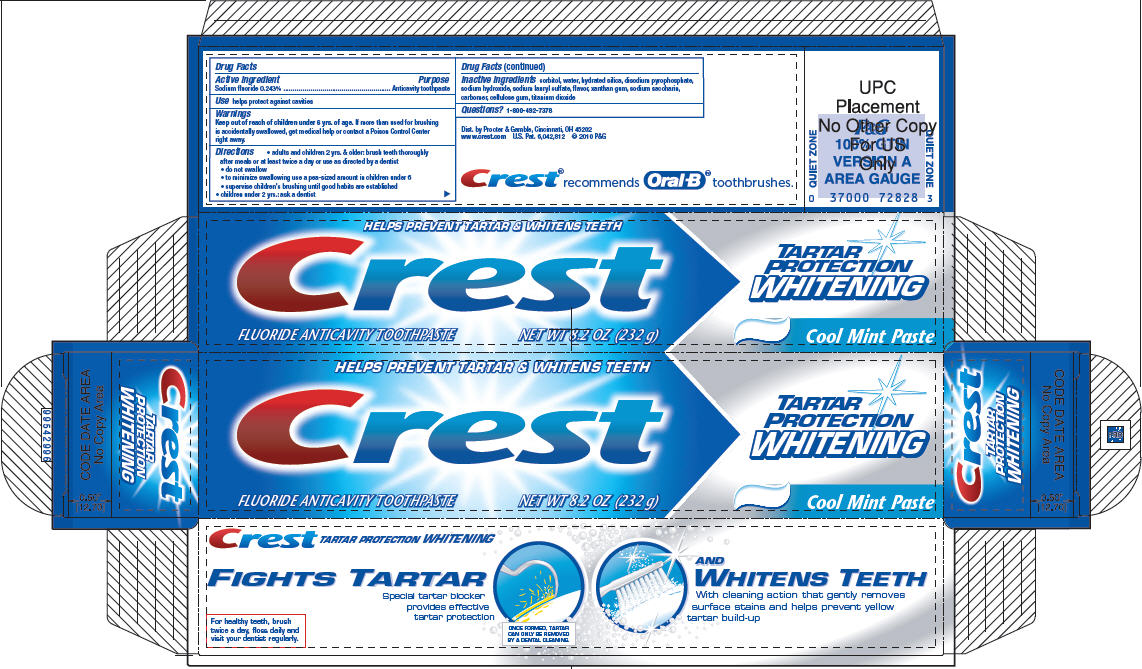 DRUG LABEL: Crest
NDC: 37000-469 | Form: PASTE, DENTIFRICE
Manufacturer: The Procter & Gamble Manufacturing Company
Category: otc | Type: HUMAN OTC DRUG LABEL
Date: 20231018

ACTIVE INGREDIENTS: SODIUM FLUORIDE 1.5 mg/1 g
INACTIVE INGREDIENTS: CARBOXYMETHYLCELLULOSE SODIUM, UNSPECIFIED FORM; HYDRATED SILICA; WATER; SODIUM PYROPHOSPHATE; SORBITOL; SODIUM HYDROXIDE; SODIUM LAURYL SULFATE; SACCHARIN SODIUM; XANTHAN GUM; TITANIUM DIOXIDE

Crest® Tartar Protection
Whitening
Cool Mint Paste

Drug Facts

Active ingredient

Sodium fluoride 0.243%

Purpose

Anticavity toothpaste

Use

helps protect against cavities

Warning

Keep out of reach of children under 6 yrs. of age. If more than used for brushing is accidentally swallowed, get medical help or contact a Poison Control Center right away.

Directions

- adults and children 2 yrs. & older: brush teeth thoroughly after meals or at least twice a day or use as directed by a dentist
  - do not swallow
  - to minimize swallowing use a pea-sized amount in children under 6
  - supervise children's brushing until good habits are established
- children under 2 yrs.: ask a dentist

Inactive ingredients

sorbitol, water, hydrated silica, disodium pyrophosphate, sodium hydroxide, sodium lauryl sulfate, flavor, xanthan gum, sodium saccharin, carbomer, cellulose gum, titanium dioxide

Questions?

1-800-492-7378

Dist. by Procter & Gamble, Cincinnati, OH 45202

PRINCIPAL DISPLAY PANEL - 232 g Tube Carton

HELPS PREVENT TARTAR & WHITENS TEETH

Crest®

FLUORIDE ANTICAVITY TOOTHPASTE
NET WT 8.2 OZ (232 g)

BAKING SODA
TARTAR

PROTECTION
WHITENING

Cool Mint Paste